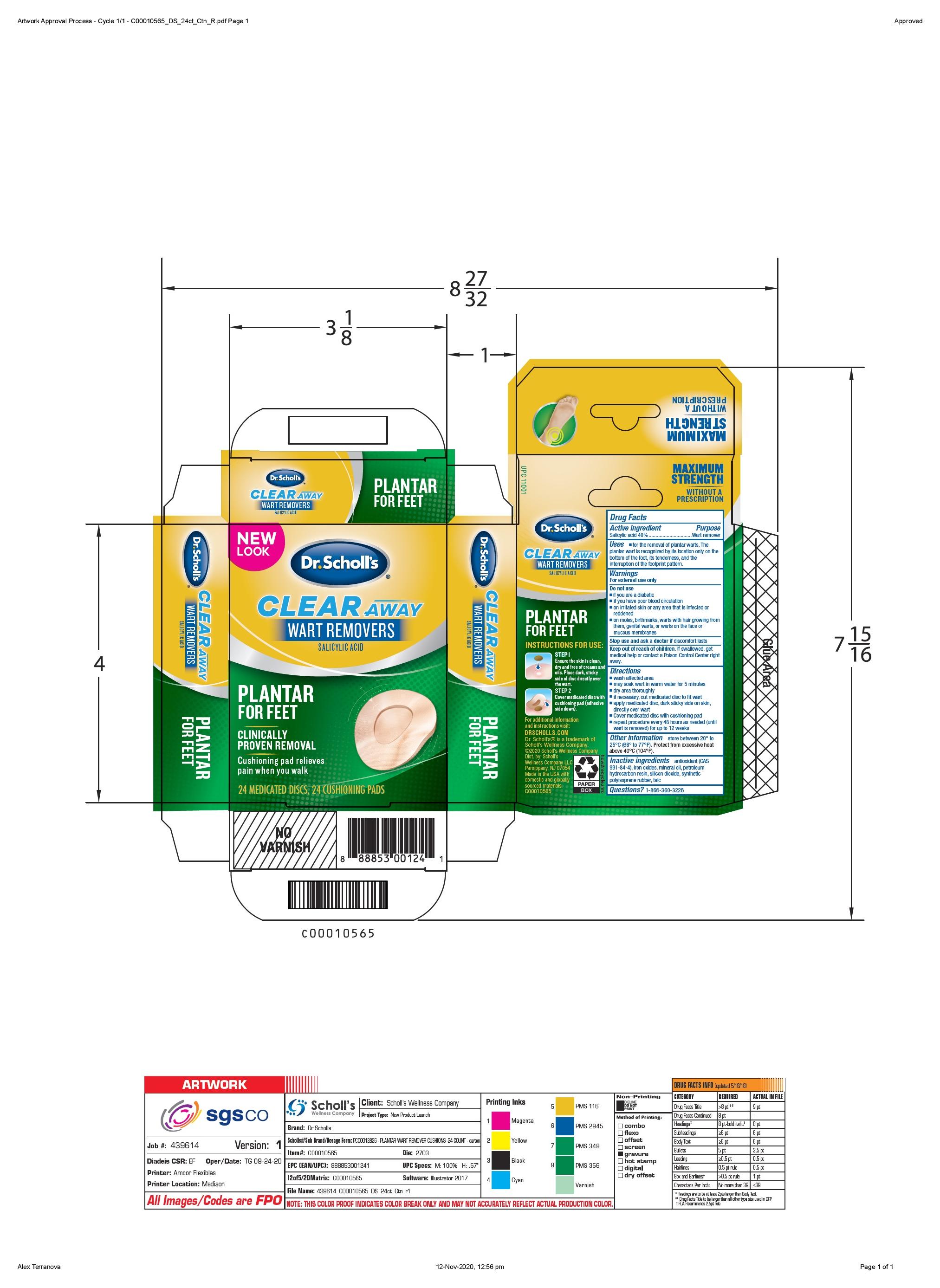 DRUG LABEL: Scholls Wellness Company LLC
NDC: 73469-0631 | Form: DISC
Manufacturer: Scholls Wellness Company LLC
Category: otc | Type: HUMAN OTC DRUG LABEL
Date: 20251221

ACTIVE INGREDIENTS: SALICYLIC ACID 4 mg/1 1
INACTIVE INGREDIENTS: TALC; SILICON DIOXIDE; MINERAL OIL

(90000126) Clear Away Wart Removers

Drug Facts

Active Ingredient Purpose

Salicylic Acid 40%.......................Wart remover

Purpose

Wart remover

Uses

for the removal of plantar warts. The plantar wart is recognized by its location only on teh bottom of the foot, its tenderness, and the interuption of the footprint pattern.

Warnings

For external use only

Do not use

if you are a diabetic
if you have poor blood circulation
on irritated skin or any area that is infected or reddened

on moles, birthmarks, warts with hair growing from them, genital warts, or warts on the face or mucous membranes.

Stop use and ask a doctor if discomfort lasts

Keep out of reach of children. If swallowed,

get medical help or contact a Poison Control Center right away.

Directions

wash affected area

may soak wart in warm water for 5 minutes

dry area thoroughly

if necessary, cut medicated disc to fit wart

apply medicated disc, dark sticky side on skin, directly over wart

cover medicated disc with enclosed cushion

repeat procedure every 48 hours as needed (until wart is removed) for up to 12 weeks

Other information

store between 20ºC to 25ºC (68º to 77ºF). Protect from excessive heat (temperatures above 40ºC (104ºF)

Inactive ingredients antioxidant
(CAS 991-84-4), iron oxides, mineral oil,

petroleum hydrocarbon resin, silicon dioxide,

synthetic polyisoprene rubber, talc

Questions? 1-866-360-3226